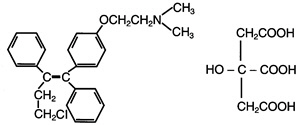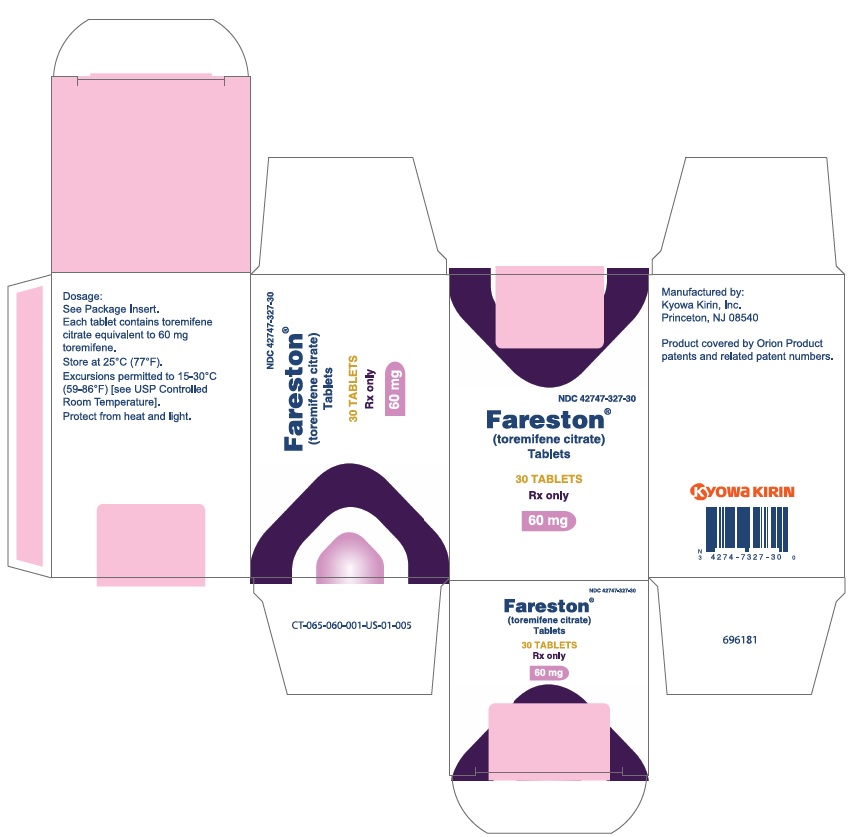 DRUG LABEL: Fareston
NDC: 42747-327 | Form: TABLET
Manufacturer: Kyowa Kirin, Inc.
Category: prescription | Type: HUMAN PRESCRIPTION DRUG LABEL
Date: 20241113

ACTIVE INGREDIENTS: TOREMIFENE CITRATE 60 mg/1 1
INACTIVE INGREDIENTS: SILICON DIOXIDE; LACTOSE MONOHYDRATE; MAGNESIUM STEARATE; MICROCRYSTALLINE CELLULOSE; POVIDONE, UNSPECIFIED; SODIUM STARCH GLYCOLATE TYPE A; STARCH, CORN; WATER

HIGHLIGHTS OF PRESCRIBING INFORMATION

These highlights do not include all the information needed to use FARESTON® safely and effectively. See full prescribing information for FARESTON®.
FARESTON® (toremifene citrate) 60 mg Tablets oral administration
Initial U.S. Approval: 1997

WARNING: QT PROLONGATION

FARESTON has been shown to prolong the QTc interval in a dose- and concentration-related manner [see Clinical Pharmacology (12.2)]. Prolongation of the QT interval can result in a type of ventricular tachycardia called Torsade de pointes, which may result in syncope, seizure, and/or death. Toremifene should not be prescribed to patients with congenital/acquired QT prolongation, uncorrected hypokalemia or uncorrected hypomagnesemia. Drugs known to prolong the QT interval and strong CYP3A4 inhibitors should be avoided [see Warnings and Precautions (5.1)].

1 INDICATIONS AND USAGE

FARESTON® is an estrogen agonist/antagonist indicated for the treatment of metastatic breast cancer in postmenopausal women with estrogen-receptor positive or unknown tumors. (1)

2 DOSAGE AND ADMINISTRATION

- 60 mg once daily, orally (2)

3 DOSAGE FORMS AND STRENGTHS

- 60 mg tablet is round, convex, unscored, uncoated, and white, or almost white, identified with TO 60 embossed on one side. (3)

4 CONTRAINDICATIONS

- Hypersensitivity to the drug (4.1)
- QT Prolongation, Hypokalemia, Hypomagnesemia (4.2)

5 WARNINGS AND PRECAUTIONS

- Prolongation of the QT Interval (5.1)
- Heptatotoxicty (5.2)
- Hypercalcemia and Tumor Flare (5.3)
- Risk of Uterine Malignancy (5.4)
- General (5.5)
- Laboratory Tests (5.6)
- Pregnancy: Fetal harm may occur when administered to a pregnant woman. Women should be advised not to become pregnant when taking FARESTON. (5.7, 8.1)
- Women of Childbearing Potential: Use effective nonhormonal contraception during FARESTON therapy. (5.8)

6 ADVERSE REACTIONS

Most common adverse reactions are hot flashes, sweating, nausea and vaginal discharge. (6.1)

To report SUSPECTED ADVERSE REACTIONS, contact Kyowa Kirin, Inc. at 1-800-305-FARESTON (1-800-305-3273) or FDA at 1-800-FDA-1088 or www.fda.gov/medwatch.

7 DRUG INTERACTIONS

- Drugs that decrease renal calcium excretion, e.g., thiazide diuretics, may increase the risk of hypercalcemia in patients receiving FARESTON. (7.1)
- Agents that prolong QT should be avoided. (7.2)
- Coadministration with a strong CYP3A4 inducer may result in a relevant decrease in FARESTON exposure and should be avoided. (7.3)
- Coadministration with a strong CYP3A4 inhibitor can result in a relevant increase in FARESTON exposure and should be avoided. (7.4)
- CYP2C9 substrates with a narrow therapeutic index such as warfarin or phenytoin with FARESTON should be used with caution and require careful monitoring. (7.6)

8 USE IN SPECIFIC POPULATIONS

- Nursing Mothers: Discontinue drug or nursing taking into account the importance of the drug to the mother. (8.2)

FULL PRESCRIBING INFORMATION

WARNING: QT PROLONGATION

FARESTON has been shown to prolong the QTc interval in a dose- and concentration-related manner [see Clinical Pharmacology (12.2)]. Prolongation of the QT interval can result in a type of ventricular tachycardia called Torsade de pointes, which may result in syncope, seizure, and/or death. Toremifene should not be prescribed to patients with congenital/acquired QT prolongation, uncorrected hypokalemia or uncorrected hypomagnesemia. Drugs known to prolong the QT interval and strong CYP3A4 inhibitors should be avoided [see Warnings and Precautions (5.1)].

1 INDICATIONS AND USAGE

FARESTON® is an estrogen agonist/antagonist indicated for the treatment of metastatic breast cancer in postmenopausal women with estrogen-receptor positive or unknown tumors.

2 DOSAGE AND ADMINISTRATION

The dosage of FARESTON is 60 mg, once daily, orally. Treatment is generally continued until disease progression is observed.

3 DOSAGE FORMS AND STRENGTHS

Tablet is 60 mg, round, convex, unscored, uncoated, and white, or almost white, identified with TO 60 embossed on one side.

4 CONTRAINDICATIONS

4.1 Hypersensitivity to the Drug

FARESTON is contraindicated in patients with known hypersensitivity to the drug.

4.2 QT Prolongation, Hypokalemia, Hypomagnesemia

Toremifene should not be prescribed to patients with congenital/acquired QT prolongation (long QT syndrome), uncorrected hypokalemia, or uncorrected hypomagnesemia.

5 WARNINGS AND PRECAUTIONS

5.1 Prolongation of the QT Interval

Toremifene has been shown to prolong the QTc interval in a dose- and concentration-related manner [see Clinical Pharmacology (12.2)]. Prolongation of the QT interval can result in a type of ventricular tachycardia called Torsade de pointes, which may result in syncope, seizure, and/or death.

Toremifene should be avoided in patients with long QT syndrome. Caution should be exercised in patients with congestive heart failure, hepatic impairment and electrolyte abnormalities. Hypokalemia or hypomagnesemia must be corrected prior to initiating toremifene and these electrolytes should be monitored periodically during therapy. Drugs that prolong the QT interval should be avoided. In patients at increased risk, electrocardiograms (ECGs) should be obtained at baseline and as clinically indicated [see Drug Interactions (7.2) and Clinical Pharmacology (12.2)].

5.2 Hepatotoxicity

Hepatotoxicity, both increases in the serum concentration for grade 3 and 4 transaminitis and hyperbilirubinemia, including jaundice, hepatitis, and non-alcoholic fatty liver disease, have also been reported in clinical trials and postmarketing with FARESTON. Liver function tests should be performed periodically. [see Adverse Reactions (6.1), Post-marketing Experience (6.2)]

5.3 Hypercalcemia and Tumor Flare

As with other antiestrogens, hypercalcemia and tumor flare have been reported in some breast cancer patients with bone metastases during the first weeks of treatment with FARESTON. Tumor flare is a syndrome of diffuse musculoskeletal pain and erythema with increased size of tumor lesions that later regress. It is often accompanied by hypercalcemia. Tumor flare does not imply failure of treatment or represent tumor progression. If hypercalcemia occurs, appropriate measures should be instituted and, if hypercalcemia is severe, FARESTON treatment should be discontinued.

5.4 Risk of Uterine Malignancy

Endometrial cancer, endometrial hypertrophy, hyperplasia, and uterine polyps have been reported in some patients treated with FARESTON. Endometrial hyperplasia of the uterus was observed in animals treated with toremifene [see Nonclinical Toxicology (13.1)]. Long-term use of FARESTON has not been established in patients with pre-existing endometrial hyperplasia. All patients should have baseline and annual gynecological examinations. In particular, patients at high risk of endometrial cancer should be closely monitored.

5.5 General

Patients with a history of thromboembolic diseases should generally not be treated with FARESTON. Patients with bone metastases should be monitored closely for hypercalcemia during the first weeks of treatment [see Warnings and Precautions (5.2)].

Leukopenia and thrombocytopenia have been reported rarely; leukocyte and platelet counts should be monitored when using FARESTON in patients with leukopenia and thrombocytopenia.

5.6 Laboratory Tests

Periodic complete blood counts, calcium levels, and liver function tests should be obtained.

5.7 Use in Pregnancy

Based on its mechanism of action in humans and findings of increased pregnancy loss and fetal malformation in animal studies, FARESTON can cause fetal harm when administered to a pregnant woman. Toremifene caused embryo-fetal toxicities at maternal doses that were lower than the 60 mg daily recommended human dose on a mg/m^2 basis. There are no adequate and well-controlled studies in pregnant women using FARESTON. If this drug is used during pregnancy, or if the patient becomes pregnant while taking this drug, the patient should be apprised of the potential hazard to the fetus [see Use in Specific Populations (8.1)].

5.8 Women of Childbearing Potential

FARESTON is indicated only in postmenopausal women. However, premenopausal women prescribed FARESTON should use effective non-hormonal contraception and should be apprised of the potential hazard to the fetus should pregnancy occur.

6 ADVERSE REACTIONS

Because clinical trials are conducted under widely varying conditions, adverse reaction rates observed in the clinical trials of a drug cannot be directly compared to rates in the clinical trials of another drug and may not reflect the rates observed in clinical practice.

6.1 Clinical Trials Experience

Adverse drug reactions are principally due to the antiestrogenic actions of FARESTON and typically occur at the beginning of treatment.

The incidences of the following eight clinical toxicities were prospectively assessed in the North American Study. The incidence reflects the toxicities that were considered by the investigator to be drug related or possibly drug related.

 | North American Study
 | FAR60 | TAM20
 | n = 221 | n = 215
Hot Flashes | 35% | 30%
Sweating | 20% | 17%
Nausea | 14% | 15%
Vaginal Discharge | 13% | 16%
Dizziness | 9% | 7%
Edema | 5% | 5%
Vomiting | 4% | 2%
Vaginal Bleeding | 2% | 4%

Approximately 1% of patients receiving FARESTON (n = 592) in the three controlled studies discontinued treatment as a result of adverse reactions (nausea and vomiting, fatigue, thrombophlebitis, depression, lethargy, anorexia, ischemic attack, arthritis, pulmonary embolism, and myocardial infarction).

Serious adverse reactions occurring in at least 1% of patients receiving FARESTON in the three major trials are listed in the table below.

Three prospective, randomized, controlled clinical studies (North American, Eastern European, and Nordic) were conducted. The patients were randomized to parallel groups receiving FARESTON 60 mg (FAR60) or tamoxifen 20 mg (TAM20) in the North American Study or tamoxifen 40 mg (TAM40) in the Eastern European and Nordic studies. The North American and Eastern European studies also included high-dose toremifene arms of 200 and 240 mg daily, respectively [see Clinical Studies (14)].

Adverse Reactions | North American |  | Eastern European |  | Nordic
 | FAR60 | TAM20 | FAR60 | TAM40 | FAR60 | TAM40
 | n=221(%) | n=215(%) | n=157(%) | n=149(%) | n=214(%) | n=201(%)
Cardiac
Cardiac Failure | 2 (1) | 1 (<1) | - | 1 (<1) | 2 (1) | 3 (1.5)
Myocardial Infarction | 2 (1) | 3 (1.5) | 1 (<1) | 2 (1) | - | 1 (<1)
Arrhythmia | - | - | - | - | 3 (1.5) | 1 (<1)
Angina Pectoris | - | - | 1 (<1) | - | 1 (<1) | 2 (1)
Ocular*
Cataracts | 22 (10) | 16 (7.5) | - | - | - | 5 (3)
Dry Eyes | 20 (9) | 16 (7.5) | - | - | - | -
Abnormal Visual Fields | 8 (4) | 10 (5) | - | - | - | 1 (<1)
Corneal Keratopathy | 4 (2) | 2 (1) | - | - | - | -
Glaucoma | 3 (1.5) | 2 (1) | 1 (<1) | - | - | 1 (<1)
Abnormal Vision/Diplopia | - | - | - | - | 3 (1.5) | -
Thromboembolic
Pulmonary Embolism | 4 (2) | 2 (1) | 1 (<1) | - | - | 1 (<1)
Thrombophlebitis | - | 2 (1) | 1 (<1) | 1 (<1) | 4 (2) | 3 (1.5)
Thrombosis | - | 1 (<1) | 1 (<1) | - | 3 (1.5) | 4 (2)
CVA/TIA | 1 (<1) | - | - | 1 (<1) | 4 (2) | 4 (2)
Elevated Liver Tests**
AST | 11 (5) | 4 (2) | 30 (19) | 22 (15) | 32 (15) | 35 (17)
Alkaline Phosphatase | 41 (19) | 24 (11) | 16 (10) | 13 (9) | 18 (8) | 31 (15)
Bilirubin | 3 (1.5) | 4 (2) | 2 (1) | 1 (<1) | 2 (1) | 3 (1.5)
Hypercalcemia | 6 (3) | 6 (3) | 1 (<1) | - | - | -
* Most of the ocular abnormalities were observed in the North American Study in which on-study and biannual ophthalmic examinations were performed. No cases of retinopathy were observed in any arm.
** Elevated defined as follows: North American Study: AST >100 IU/L; alkaline phosphatase >200 IU/L; bilirubin > 2 mg/dL. Eastern European and Nordic studies: AST, alkaline phosphatase, and bilirubin - WHO Grade 1 (1.25 times the upper limit of normal).

Other adverse reactions included leukopenia and thrombocytopenia, skin discoloration or dermatitis, constipation, dyspnea, paresis, tremor, vertigo, pruritus, anorexia, reversible corneal opacity (corneal verticulata), asthenia, alopecia, depression, jaundice, and rigors.

The incidence of AST elevations was greater in the 200 and 240 mg FARESTON dose arms than in the tamoxifen arms. Higher doses of FARESTON were also associated with an increase in nausea.

Approximately 4% of patients were withdrawn for toxicity from the high-dose FARESTON treatment arms. Reasons for withdrawal included hypercalcemia, abnormal liver function tests, and one case each of toxic hepatitis, depression, dizziness, incoordination, ataxia, blurry vision, diffuse dermatitis, and a constellation of symptoms consisting of nausea, sweating, and tremor.

6.2 Post-marketing Experience

The following adverse reactions were identified during post approval use of FARESTON. Because these reactions are reported voluntarily from a population of uncertain size, it is not always possible to reliably estimate their frequency or establish a causal relationship to drug exposure.

Adverse reactions reported during post approval use of FARESTON have been consistent with clinical trial experience. The most frequently reported adverse reactions related to FARESTON use since market introduction include hot flash, sweating, nausea, and vaginal discharge.

Hepatotoxicity [see Warnings and Precautions (5.2)]

Risk of Uterine Malignancy [see Warnings and Precautions (5.4)]

Hypertriglyceridemia

7 DRUG INTERACTIONS

7.1 Drugs that Decrease Renal Calcium Excretion

Drugs that decrease renal calcium excretion, e.g., thiazide diuretics, may increase the risk of hypercalcemia in patients receiving FARESTON.

7.2 Agents that Prolong QT

The administration of FARESTON with agents that have demonstrated QT prolongation as one of their pharmacodynamic effects should be avoided. Should treatment with any of these agents be required, it is recommended that therapy with FARESTON be interrupted. If interruption of treatment with FARESTON is not possible, patients who require treatment with a drug that prolongs QT should be closely monitored for prolongation of the QT interval. Agents generally accepted to prolong QT interval include Class 1A (e.g., quinidine, procainamide, disopyramide) and Class III (e.g., amiodarone, sotalol, ibutilide, dofetilide) antiarrhythmics; certain antipsychotics (e.g., thioridazine, haloperidol); certain antidepressants (e.g., venlafaxine, amitriptyline); certain antibiotics (e.g., erythromycin, clarithromycin, levofloxacin, ofloxacin); and certain anti-emetics (e.g., ondansetron, granisetron). In patients at increased risk, electrocardiograms (ECGs) should be obtained and patients monitored as clinically indicated [see Boxed Warning and Warnings and Precautions (5.1)].

7.3 Effect of Strong CYP3A4 Inducers on Toremifene

Strong CYP3A4 enzyme inducers, such as dexamethasone, phenytoin, carbamazepine, rifampin, rifabutin, phenobarbital, St. John's Wort, lower the steady-state concentration of toremifene in serum.

7.4 Effect of Strong CYP3A4 Inhibitors on Toremifene

In a study of 18 healthy subjects, 80 mg toremifene once daily coadministered with 200 mg of ketoconazole twice daily increased the toremifene Cmax and AUC by 1.4- and 2.9-fold, respectively. N-demethyltoremifene Cmax and AUC were reduced by 56% and 20%, respectively.

The administration of FARESTON with agents that are strong CYP3A4 inhibitors (e.g., ketoconazole, itraconazole, clarithromycin, atazanavir, indinavir, nefazodone, nelfinavir, ritonavir, saquinavir, telithromycin, and voriconazole) increase the steady-state concentration in serum and should be avoided. Grapefruit juice may also increase plasma concentrations of toremifene and should be avoided. Should treatment with any of these agents be required, it is recommended that therapy with FARESTON be interrupted. If interruption of treatment with FARESTON is not possible, patients who require treatment with a drug that strongly inhibits CYP3A4 should be closely monitored for prolongation of the QT interval [see Boxed Warning and Warnings and Precautions (5.1)].

7.5 Effect of Toremifene on CYP3A4 Substrates

In a study of 20 healthy subjects, 2 mg midazolam once daily (days 6 and 18) coadministered with toremifene as a 480 mg loading dose followed by 80 mg once daily for 16 days. Following coadministration on days 6 and 18 relevant increases in midazolam and α-hydroxymidazolam Cmax and AUC were not observed. Following coadministration on day 18 midazolam and α-hydroxymidazolam Cmax and AUC were reduced by less than 20%.

Clinically relevant exposure changes in sensitive substrates due to inhibition or induction of CYP3A4 by toremifene appear unlikely.

7.6 Effect of Toremifene on CYP2C9 Substrates

In a study of 20 healthy subjects, 500 mg tolbutamide once daily (days 7 and 19) coadministered with toremifene as a 480 mg loading dose followed by 80 mg once daily for 16 days. Following coadministration on days 7 and 19 plasma tolbutamide Cmax and AUC were increased by less than 30%. A reduction of similar magnitude was observed for hydroxytolbutamide and carboxytolbutamide Cmax and AUC.

Toremifene is a weak inhibitor of CYP2C9. Concomitant use of CYP2C9 substrates with a narrow therapeutic index such as warfarin or phenytoin with FARESTON should be done with caution and requires careful monitoring (e.g., substrate concentrations (if possible), appropriate laboratory markers, and signs and symptoms of increased exposure).

8 USE IN SPECIFIC POPULATIONS

8.1 Pregnancy

Pregnancy Category D [see Warnings and Precautions (5.7).]

Based on its mechanism of action in humans and findings of increased pregnancy loss and fetal malformation in animal studies, FARESTON can cause fetal harm when administered to a pregnant woman. Toremifene caused embryo-fetal toxicities at maternal doses that were lower than the 60 mg daily recommended human dose on a mg/m^2 basis. There are no adequate and well-controlled studies in pregnant women using FARESTON. If this drug is used during pregnancy, or if the patient becomes pregnant while taking this drug, the patient should be apprised of the potential hazard to the fetus.

In animal studies, toremifene crossed the placenta and accumulated in the rodent fetus. Administration of toremifene to pregnant rats during organogenesis at doses of approximately 6% the daily maximum recommended human dose of 60 mg (on a mg/m^2 basis) resulted in signs of maternal toxicity and increased preimplantation loss, increased resorptions, reduced fetal weight, and fetal anomalies. Fetal anomalies include malformation of limbs, incomplete ossification, misshapen bones, ribs/spine anomalies, hydroureter, hydronephrosis, testicular displacement, and subcutaneous edema. Maternal toxicity may have contributed to these adverse embryo-fetal effects. Similar embryo-fetal toxicities occurred in rabbits that received toremifene at doses approximately 40% the daily recommended human dose of 60 mg (on a mg/m^2 basis). Findings in rabbits included increased preimplantation loss, increased resorptions, and fetal anomalies, including incomplete ossification and anencephaly.

Animal doses resulting in embryo-fetal toxicities were ≥1.0 mg/kg/day in rats and ≥1.25 mg/kg/day in rabbits.

In rodent models of fetal reproductive tract development, toremifene produced inhibition of uterine development in female pups similar to effects seen with diethylstilbestrol (DES) and tamoxifen. The clinical relevance of these changes is not known. Neonatal rodent studies have not been conducted to assess the potential for toremifene to cause other DES-like effects in offspring (i.e., vaginal adenosis). Vaginal adenosis in animals occurred following treatment with other drugs of this class and has been observed in women exposed to diethylstilbestrol in utero.

8.2 Nursing Mothers

It is not known if toremifene is excreted in human milk. Toremifene is excreted in the milk of lactating rats. Because many drugs are excreted in human milk and because of the potential for serious adverse reactions in nursing infants from FARESTON, a decision should be made to either discontinue nursing or discontinue the drug, taking into account the importance of the drug to the mother.

8.3 Pediatric Use

There is no indication for use of FARESTON in pediatric patients.

8.4 Geriatric Use

The pharmacokinetics of toremifene were studied in 10 healthy young males and 10 elderly females following a single 120 mg dose under fasting conditions. Increases in the elimination half-life (4.2 versus 7.2 days) and the volume of distribution (457 versus 627 L) of toremifene were seen in the elderly females without any change in clearance or AUC.

The median ages in the three controlled studies ranged from 60 to 66 years. No significant age-related differences in FARESTON effectiveness or safety were noted.

8.5 Renal Impairment

The pharmacokinetics of toremifene and N-demethyltoremifene were similar in normals and in patients with impaired kidney function.

8.6 Hepatic Impairment

The mean elimination half-life of toremifene was increased by less than twofold in 10 patients with hepatic impairment (cirrhosis or fibrosis) compared to subjects with normal hepatic function. The pharmacokinetics of N-demethyltoremifene were unchanged in these patients. Ten patients on anticonvulsants (phenobarbital, clonazepam, phenytoin, and carbamazepine) showed a twofold increase in clearance and a decrease in the elimination half-life of toremifene.

8.7 Race

The pharmacokinetics of toremifene in patients of different races has not been studied.

Fourteen percent of patients in the North American Study were non-Caucasian. No significant race-related differences in FARESTON effectiveness or safety were noted.

10 OVERDOSAGE

Lethality was observed in rats following single oral doses that were ≥1000 mg/kg (about 150 times the recommended human dose on a mg/m^2 basis) and was associated with gastric atony/dilatation leading to interference with digestion and adrenal enlargement.

Vertigo, headache, and dizziness were observed in healthy volunteer studies at a daily dose of 680 mg for 5 days. The symptoms occurred in two of the five subjects during the third day of the treatment and disappeared within 2 days of discontinuation of the drug. No immediate concomitant changes in any measured clinical chemistry parameters were found. In a study in postmenopausal breast cancer patients, toremifene 400 mg/m^2/day caused dose-limiting nausea, vomiting, and dizziness, as well as reversible hallucinations and ataxia in one patient.

Theoretically, overdose may be manifested as an increase of antiestrogenic effects, such as hot flashes; estrogenic effects, such as vaginal bleeding; or nervous system disorders, such as vertigo, dizziness, ataxia, and nausea. There is no specific antidote and the treatment is symptomatic.

11 DESCRIPTION

FARESTON (toremifene citrate) Tablets for oral administration each contain 88.5 mg of toremifene citrate, which is equivalent to 60 mg toremifene.

FARESTON is an estrogen agonist/antagonist. The chemical name of toremifene is: 2-{p-[(Z)-4-chloro-1,2-diphenyl-1-butenyl]phenoxy}-N,N-dimethylethylamine citrate (1:1). The structural formula is:

and the molecular formula is C26H28ClNO • C6H8O7. The molecular weight of toremifene citrate is 598.10. The pKa is 8.0. Water solubility at 37°C is 0.63 mg/mL and in 0.02N HCl at 37°C is 0.38 mg/mL.

FARESTON is available only as tablets for oral administration. Inactive ingredients: colloidal silicon dioxide, lactose, magnesium stearate, microcrystalline cellulose, povidone, sodium starch glycolate, and starch.

12 CLINICAL PHARMACOLOGY

12.1 Mechanism of Action

Toremifene is a nonsteroidal triphenylethylene derivative. Toremifene binds to estrogen receptors and may exert estrogenic, antiestrogenic, or both activities, depending upon the duration of treatment, animal species, gender, target organ, or endpoint selected. In general, however, nonsteroidal triphenylethylene derivatives are predominantly antiestrogenic in rats and humans and estrogenic in mice. In rats, toremifene causes regression of established dimethylbenzanthracene (DMBA)-induced mammary tumors. The antitumor effect of toremifene in breast cancer is believed to be mainly due to its antiestrogenic effects, i.e., its ability to compete with estrogen for binding sites in the cancer, blocking the growth-stimulating effects of estrogen in the tumor.

12.2 Pharmacodynamics

Toremifene causes a decrease in the estradiol-induced vaginal cornification index in some postmenopausal women, indicative of its antiestrogenic activity. Toremifene also has estrogenic activity as shown by decreases in serum gonadotropin concentrations (FSH and LH).

Effects on Cardiac Electrophysiology

The effect of 20 mg, 80 mg, and 300 mg of toremifene on QT interval was evaluated in a double-blind, randomized study in healthy male subjects aged 18 to 45 years. The QT interval was measured at steady state of toremifene (Day 5 of dosing), including the time of peak plasma concentration (Tmax), at 13 time points (4 ECGs/time point) over 24 hours post dose in a time matched analysis. The 300 mg dose of toremifene (approximately five times the highest recommended dose 60 mg) was chosen because this dose produces exposure to toremifene that will cover the expected exposures that may result from potential drug interactions and hepatic impairment [see Drug Interactions (7.2)].

Dose and concentration-related increases in the QTc interval and T wave changes were observed (see Table 1). These effects are believed to be caused by toremifene and N-demethyltoremifene. Toremifene had no effects on heart rate, PR and QRS interval duration [see Boxed Warning and Warnings and Precautions (5.1)].

Table 1: QTc Prolongation in Healthy Male Volunteers
Treatment Arm | Mean (90% CI) ΔΔQTc, ms | ΔQTc > 60 ms (n, %) | QTc > 500 ms (n, %)
Toremifene 20 mg (N = 47) | 7 (0.9, 13.6) | 0 | 0
Toremifene 80 mg (N = 47) | 26 (21.1, 31.2) | 2 (4.3%) | 0
Toremifene 300 mg (N = 48) | 65 (60.1, 69.2) | 43 (89.6%) | 5 (10.4%)

12.3 Pharmacokinetics

Absorption - Toremifene is well absorbed after oral administration and absorption is not influenced by food. Peak plasma concentrations are obtained within 3 hours. Toremifene displays linear pharmacokinetics after single oral doses of 10 to 680 mg. After multiple dosing, dose proportionality was observed for doses of 10 to 400 mg. Steady state concentrations were reached in about 4-6 weeks.

Distribution - Toremifene has an apparent volume of distribution of 580 L and binds extensively (>99.5%) to serum proteins, mainly albumin.

Metabolism - Toremifene is extensively metabolized, principally by CYP3A4 to N-demethyltoremifene which is also antiestrogenic but with weak in vivo antitumor potency. Serum concentrations of N-demethyltoremifene are 2 to 4 times higher than toremifene at steady state.

Following multiple dosing with toremifene in 20 healthy volunteers, plasma toremifene exposure was lower on Day 17 compared to Day 5 by approximately 14%. N-demethyltoremifene exposure was higher on Day 17 compared to Day 5 by approximately 80%. Based on these data and an in vitro induction study in human hepatocytes, auto-induction of CYP3A4 by toremifene is likely. The effect of auto-induction on efficacy was likely captured following prolonged dosing in the clinical studies.

Elimination - The plasma concentration time profile of toremifene declines biexponentially after absorption with a mean distribution half-life of about 4 hours and an elimination half-life of about 5 days. Elimination half-lives of major metabolites, N-demethyltoremifene and (Deaminohydroxy) toremifene, were 6 and 4 days, respectively. Mean total clearance of toremifene was approximately 5 L/h. Toremifene is eliminated as metabolites primarily in the feces, with about 10% excreted in the urine during a 1-week period. Elimination of toremifene is slow, in part because of enterohepatic circulation.

Renal insufficiency - The pharmacokinetics of toremifene and N-demethyltoremifene were similar in normals and patients with impaired kidney function.

Hepatic insufficiency - The mean elimination half-life of toremifene was increased by less than twofold in 10 patients with hepatic impairment (cirrhosis or fibrosis) compared to subjects with normal hepatic function. The pharmacokinetics of N-demethyltoremifene were unchanged in these patients. Ten patients on anticonvulsants (phenobarbital, clonazepam, phenytoin, and carbamazepine) showed a twofold increase in clearance and a decrease in the elimination half-life of toremifene.

Geriatric patients - The pharmacokinetics of toremifene were studied in 10 healthy young males and 10 elderly females following a single 120 mg dose under fasting conditions. Increases in the elimination half-life (4.2 versus 7.2 days) and the volume of distribution (457 versus 627 L) of toremifene were seen in the elderly females without any change in clearance or AUC. The median ages in the three controlled studies ranged from 60 to 66 years. No significant age-related differences in FARESTON effectiveness or safety were noted.

Food - The rate and extent of absorption of FARESTON are not influenced by food; thus FARESTON may be taken with or without food.

Race - The pharmacokinetics of toremifene in patients of different races has not been studied. Fourteen percent of patients in the North American Study were non-Caucasian. No significant race-related differences in FARESTON effectiveness or safety were noted.

13 NONCLINICAL TOXICOLOGY

13.1 Carcinogenesis, Mutagenesis, and Impairment of Fertility

Conventional carcinogenesis studies in rats at doses of 0.12 to 12 mg/kg/day (approximately 1/50 to 2 times the daily maximum recommended human dose of 60 mg, on a mg/m^2 basis) for up to 2 years did not show evidence of carcinogenicity. Studies in mice at doses of 1.0 to 30.0 mg/kg/day (approximately 1/15 to 2 times the daily maximum recommended human dose of 60 mg, on a mg/m^2 basis) for up to 2 years revealed increased incidence of ovarian and testicular tumors and increased incidence of osteoma and osteosarcoma. The significance of the mouse findings is uncertain because of the different role of estrogens in mice and the estrogenic effect of toremifene in mice. An increased incidence of ovarian and testicular tumors in mice has also been observed with other human estrogen agonists/antagonists that have primarily estrogenic activity in mice. Endometrial hyperplasia of the uterus was observed in monkeys following 52 weeks of treatment at ≥1 mg/kg and in dogs following 16 weeks of treatment at ≥3 mg/kg with toremifene (approximately 1/3 and 1.4 times, respectively, the daily maximum recommended human dose of 60 mg, on a mg/m^2 basis).

Toremifene has not been shown to be mutagenic in in vitro tests (Ames and E. coli bacterial tests). Toremifene is clastogenic in vitro (chromosomal aberrations and micronuclei formation in human lymphoblastoid MCL-5 cells) and in vivo (chromosomal aberrations in rat hepatocytes).

Toremifene produced impairment of fertility and conception in male and female rats at doses ≥25.0 and 0.14 mg/kg/day, respectively (approximately 4 times and 1/50 the daily maximum recommended human dose of 60 mg, on a mg/m^2 basis). At these doses, sperm counts, fertility index, and conception rate were reduced in males with atrophy of seminal vesicles and prostate. In females, fertility and reproductive indices were markedly reduced with increased pre- and post-implantation loss. In addition, offspring of treated rats exhibited depressed reproductive indices. Toremifene produced ovarian atrophy in dogs administered doses ≥3 mg/kg/day (approximately 1.5 times the daily maximum recommended human dose of 60 mg, on a mg/m^2 basis) for 16 weeks. Cystic ovaries and reduction in endometrial stromal cellularity were observed in monkeys at doses ≥1 mg/kg/day (about 1/3 the daily maximum recommended human dose of 60 mg, on a mg/m^2 basis) for 52 weeks.

14 CLINICAL STUDIES

Three prospective, randomized, controlled clinical studies (North American, Eastern European, and Nordic) were conducted to evaluate the efficacy of FARESTON for the treatment of breast cancer in postmenopausal women. The patients were randomized to parallel groups receiving FARESTON 60 mg (FAR60) or tamoxifen 20 mg (TAM20) in the North American Study or tamoxifen 40 mg (TAM40) in the Eastern European and Nordic studies. The North American and Eastern European studies also included high-dose toremifene arms of 200 and 240 mg daily, respectively. The studies included postmenopausal patients with estrogen-receptor (ER) positive or estrogen-receptor (ER) unknown metastatic breast cancer. The patients had at least one measurable or evaluable lesion. The primary efficacy variables were response rate (RR) and time to progression (TTP). Survival (S) was also determined. Ninety-five percent confidence intervals (95% CI) were calculated for the difference in RR between FAR60 and TAM groups and the hazard ratio (relative risk for an unfavorable event, such as disease progression or death) between TAM and FAR60 for TTP and S.

Two of the 3 studies showed similar results for all effectiveness endpoints. However, the Nordic Study showed a longer time to progression for tamoxifen (see table).

Clinical Studies
Study | North American |  | Eastern European |  | Nordic
Treatment Group | FAR60 | TAM20 | FAR60 | TAM40 | FAR60 | TAM40
No. Patients | 221 | 215 | 157 | 149 | 214 | 201
Responses
CR^1 + PR^2 | 14 + 33 | 11 + 30 | 7 + 25 | 3 + 28 | 19 + 48 | 19 + 56
RR^3 (CR + PR)% | 21.3 | 19.1 | 20.4 | 20.8 | 31.3 | 37.3
Difference in RR | 2.2 |  | -0.4 |  | -6.0
95% CI^4 for Difference in RR | -5.8 to 10.2 |  | -9.5 to 8.6 |  | -15.1 to 3.1
Time to Progression (TTP)
Median TTP (mo.) | 5.6 | 5.8 | 4.9 | 5.0 | 7.3 | 10.2
Hazard Ratio (TAM/FAR) | 1.01 |  | 1.02 |  | 0.80
95% CI^4 for Hazard Ratio (%) | 0.81 to 1.26 |  | 0.79 to 1.31 |  | 0.64 to 1.00
Survival (S)
Median S (mo.) | 33.6 | 34.0 | 25.4 | 23.4 | 33.0 | 38.7
Hazard Ratio (TAM/FAR) | 0.94 |  | 0.96 |  | 0.94
95% CI^4 for Hazard Ratio (%) | 0.74 to 1.24 |  | 0.72 to 1.28 |  | 0.73 to 1.22
^1CR = complete response; ^2PR = partial response; ^3RR = response rate; ^4CI = confidence interval

The high-dose groups, toremifene 200 mg daily in the North American Study and 240 mg daily in the Eastern European Study, were not superior to the lower toremifene dose groups, with response rates of 22.6% and 28.7%, median times to progression of 5.6 and 6.1 months, and median survivals of 30.1 and 23.8 months, respectively. The median treatment duration in the three pivotal studies was 5 months (range 4.2-6.3 months).

16 SUPPLIED/STORAGE AND HANDLING

FARESTON Tablets, containing toremifene citrate in an amount equivalent to 60 mg of toremifene, are round, convex, unscored, uncoated, and white, or almost white.

FARESTON Tablets are identified with TO 60 embossed on one side.

FARESTON Tablets are available as:
NDC 42747-327-30 bottles of 30
NDC 42747-327-72 samples of 7

Store at 25°C (77°F).
Excursions permitted to 15-30°C (59-86°F)
[See USP Controlled Room Temperature.]
Protect from heat and light.

17 PATIENT COUNSELING INFORMATION

Vaginal bleeding has been reported in patients using FARESTON. Patients should be informed about this and instructed to contact their physician if such bleeding or other gynecological symptoms (changes in vaginal discharge, pelvic pain or pressure) occur. Patients should have a gynecological examination prior to initiation of therapy and at regular intervals while on therapy.

Liver disorders including transaminits grade 3 and 4, hyperbilirubinemia with jaundice have been reported in patients using FARESTON. Patients should have liver function tests performed periodically while on therapy.

FARESTON may harm the fetus and increase the risk for pregnancy loss [see Warnings and Precautions (5.7) and Use in Specific Populations (8.1)].

Premenopausal women using FARESTON should use nonhormonal contraception during treatment and should be apprised of the potential hazard to the fetus should pregnancy occur [see Warnings and Precautions (5.8)].

Patients with bone metastases should be informed about the typical signs and symptoms of hypercalcemia and instructed to contact their physician for further assessment if such signs or symptoms occur.

Patients who must take medications known to prolong the QT interval, or potent CYP3A4 inhibitors, should be informed of the effect of toremifene on QT interval. Toremifene has been shown to prolong the QTc interval in a dose-related manner [see Boxed Warning, Warnings and Precautions (5.1), and Clinical Pharmacology (12.2)].

Specific interactions with foods that inhibit CYP3A4, including grapefruit juice, have not been studied but may increase toremifene concentrations. Patients should avoid grapefruit products and other foods that are known to inhibit CYP3A4 during FARESTON treatment.

Certain other medicines, including over-the-counter medications or herbal supplements (such as St. John's Wort) and toremifene, can reduce concentrations of co-administered drugs [see Drug Interactions (7.3)].

Distributed by:
Kyowa Kirin, Inc.
Princeton, NJ 08540
Product covered by Orion Product Patents and related patent numbers
© 2023 Kyowa Kirin, Inc.
All rights reserved.

PRINCIPAL DISPLAY PANEL - 60 mg Tablet Carton

NDC 42747-327-30

Fareston®
(toremifene citrate)
Tablets

30 TABLETS

Rx only

60 mg

KYOWA KIRIN